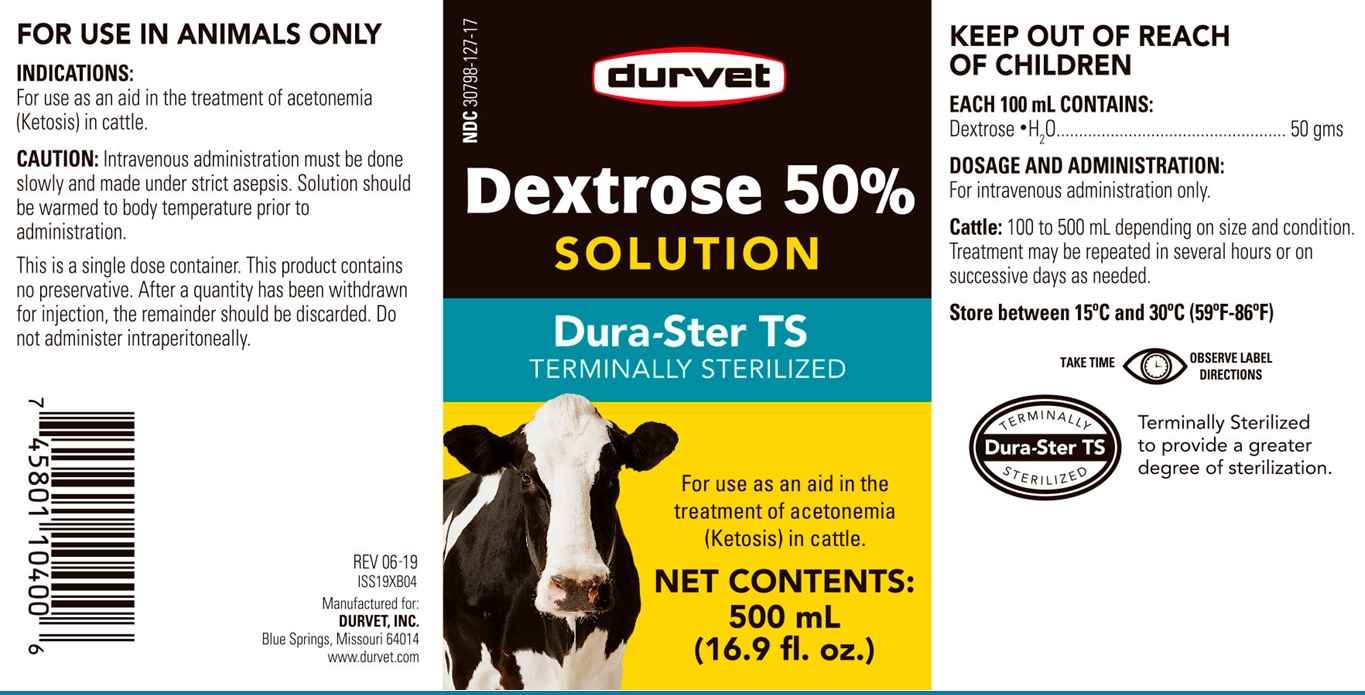 DRUG LABEL: Dextrose
NDC: 30798-127 | Form: INJECTION, SOLUTION
Manufacturer: Durvet
Category: animal | Type: OTC ANIMAL DRUG LABEL
Date: 20191107

ACTIVE INGREDIENTS: DEXTROSE MONOHYDRATE 50 g/100 mL

Dextrose 50%

For intravenous administration only.

Cattle. 100 to 500 mL depending on size and condition. Treatment may be repeated in several hours or on successive days as needed.

CAUTIONS

Intravenous administration must be done slowly and made under stric asepsis. Solution should be warmed to body temperature prior to administration.

This is a single dose container. This product contains no preservative. After a quantity has been withdrawn for injection, the remainder should be discarded. Do not administer intraperitoneally

ACTIVE INGREDIENTS:

Each 100 mL contains:

Dextrose . H2O .......................... 50 gms.

STORAGE AND HANDLING

Store between 15°C and 30°C (59°F and 86°F)

INDICATIONS:

For use as an aid in the treatment of acetonemia (ketosis) in cattle.

KEEP OUT OF REACH OF CHILDREN

VETERINARY INDICATIONS

FOR USE IN ANIMALS ONLY

SAFE HANDLING WARNING

TAKE TIME. OBSERVE LABEL DIRECTIONS

INFORMATION FOR OWNERS/CAREGIVERS

REV 06-19

ISS19XB04

Manufactured for:

DURVET, INC.

Blue Springs, Missouri 64014

www.durvet.com

Principal Display Panel

NDC 30798-127-17

durvet

DEXTROSE 50% SOLUTION

Dura-Ster TS

TERMINALLY STERILIZED

For use as an aid in the treatment of acetonemia (Ketosis) in cattle.

NET CONTENTS: 500 mL

(16.9 fl. oz.)